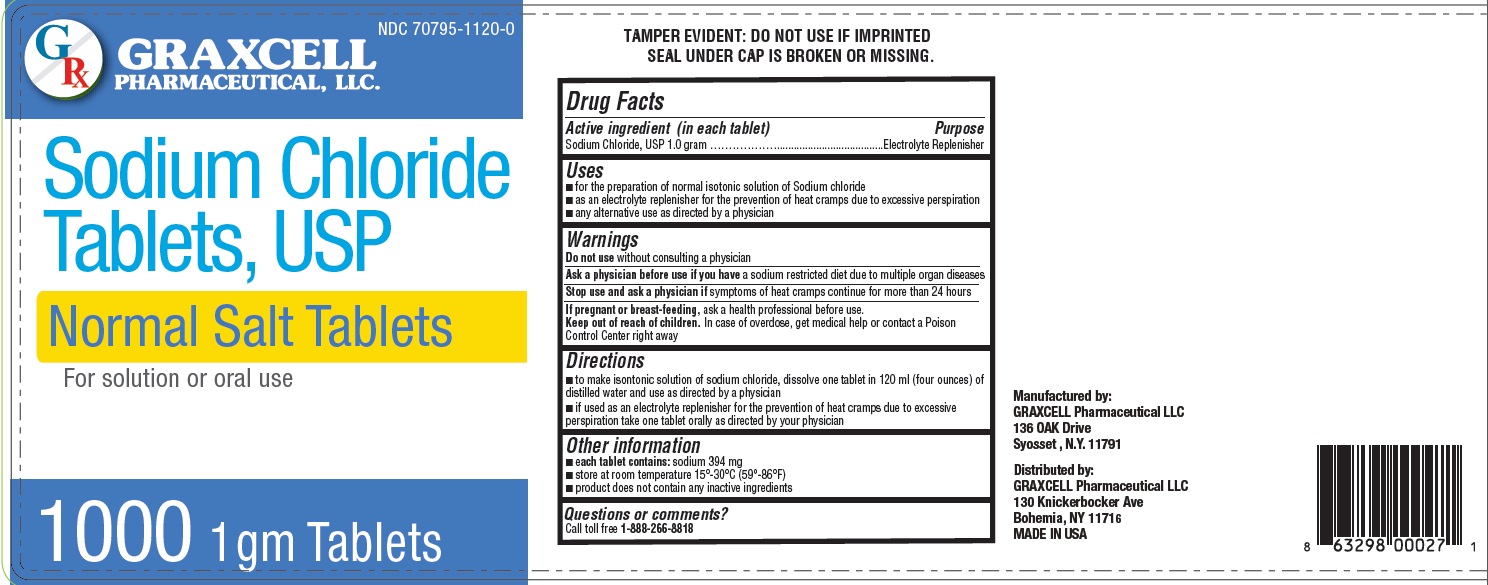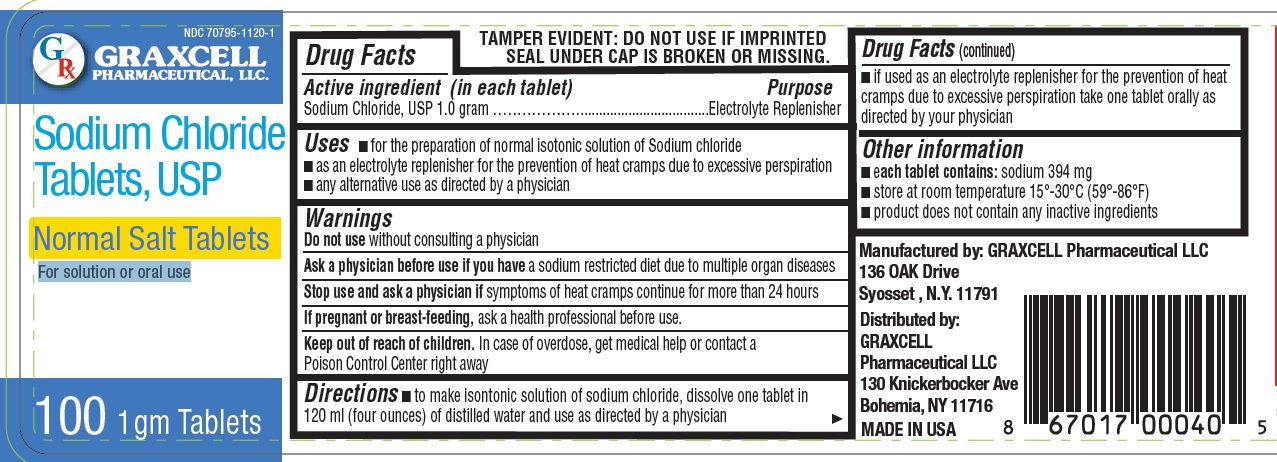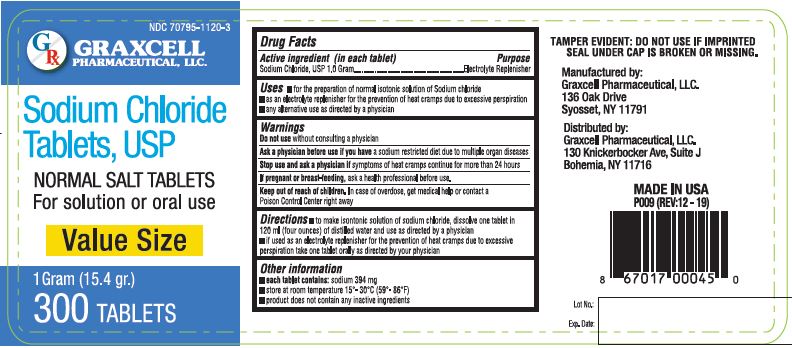 DRUG LABEL: Normal Salt
NDC: 70795-1120 | Form: TABLET
Manufacturer: GRAXCELL PHARMACEUTICAL, LLC
Category: otc | Type: HUMAN OTC DRUG LABEL
Date: 20251225

ACTIVE INGREDIENTS: SODIUM CHLORIDE 1 g/1 1
INACTIVE INGREDIENTS: POWDERED CELLULOSE

Sodium Chloride Tablets, USP; Normal Salt Tablets (1 gram), 70795-1120

Active ingredient (in each tablet)

Sodium Chloride, USP 1.0 gram

Purpose

Electrolyte Replenisher

Uses

- for the preparation of normal isotonic solution of Sodium chloride
- as an electrolyte replenisher for the prevention of heat cramps due to excessive perspiration
- any alternative use as directed by a physician

Warnings

Enter section text here

Do not use

without consulting a physician

Ask a physician before use

if you have a sodium restricted diet due to multiple organ diseases

Stop use and ask a physician

If symptoms of heat cramps continue for more than 24 hours

If pregnant or breast-feeding

ask a health professional before use.

Keep out of reach of children.

In case of overdose, get medical help or contact a Poison Control Center right away

Directions

- to make isontonic solution of sodium chloride, dissolve one tablet in 120 ml (four ounces) of distilled water and use as directed by a physician
- if used as an electrolyte replenisher for the prevention of heat cramps due to excessive perspiration take one tablet orally as
  directed by your physician

Other information

- each tablet contains: sodium 394 mg
- store at room temperature 15°-30°C (59°-86°F)
- product does not contain any inactive ingredients

INACTIVE INGREDIENTS

NONE